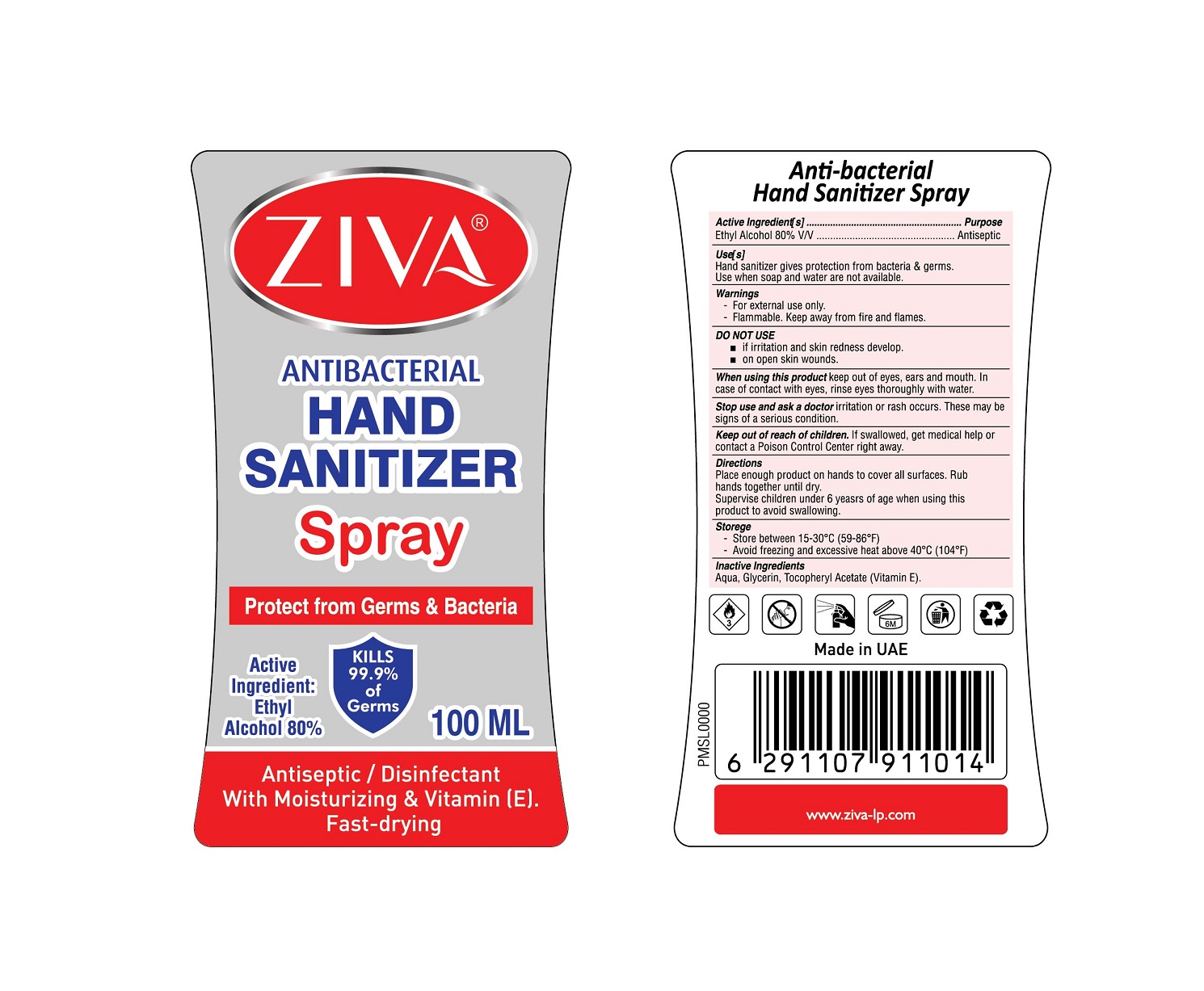 DRUG LABEL: ZIVA HAND SANITIZER
NDC: 81450-004 | Form: SPRAY
Manufacturer: Ziva Wetwipes FZCo
Category: otc | Type: HUMAN OTC DRUG LABEL
Date: 20231005

ACTIVE INGREDIENTS: ALCOHOL 80 mL/100 mL
INACTIVE INGREDIENTS: GLYCERIN; WATER; .ALPHA.-TOCOPHEROL ACETATE

Drug Facts

Active Ingredient (s)

Ethyl Alcohol 80% V/V

Purpose

Antiseptic

Use(s)

Hand sanitizer gives protection from bacteria & germs.

Use when soap and water are not available

Warnings

-For external use only.
-Flammable, keep away from the flames.

DO NOT USE

If irritation and skin redness develop.
On open skin wounds

When using this product Keep out of eyes, ears and mouth, In case of contact with eyes, rinse eyes thoroughly with water.

Stop use and ask for a doctor Irritation or rash occurs. These may be signs of a serious condition.

Keep out of reach of children. If swallowed, get medical help or contact a Poison Control Center right away.

Directions

Place enough product on hands to cover all surfaces. Rub hands together until dry.
Supervise children under 6 years of age when using this product to avoid swallowing.

Storage

Store between 15-30° C (59-86° F)
Avoid freezing and excessive heat above 40° C (104° F)

Inactive Ingredients.

Aqua, Glycerin, Tocopheryl Acetate (Vitamin E).